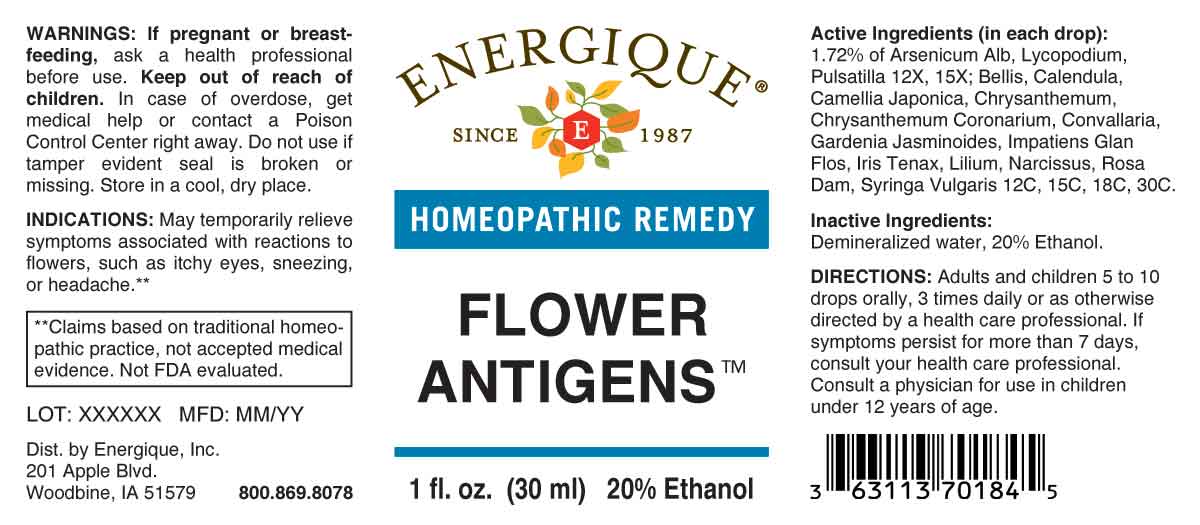 DRUG LABEL: Flower Antigens
NDC: 44911-0324 | Form: LIQUID
Manufacturer: Energique, Inc.
Category: homeopathic | Type: HUMAN OTC DRUG LABEL
Date: 20230804

ACTIVE INGREDIENTS: ARSENIC TRIOXIDE 12 [hp_X]/1 mL; LYCOPODIUM CLAVATUM SPORE 12 [hp_X]/1 mL; PULSATILLA PRATENSIS WHOLE 12 [hp_X]/1 mL; BELLIS PERENNIS WHOLE 12 [hp_C]/1 mL; CALENDULA OFFICINALIS FLOWERING TOP 12 [hp_C]/1 mL; CAMELLIA JAPONICA FLOWER 12 [hp_C]/1 mL; GLEBIONIS CORONARIA WHOLE 12 [hp_C]/1 mL; LEUCANTHEMUM VULGARE WHOLE 12 [hp_C]/1 mL; CONVALLARIA MAJALIS 12 [hp_C]/1 mL; GARDENIA JASMINOIDES FLOWER 12 [hp_C]/1 mL; IMPATIENS GLANDULIFERA FLOWER 12 [hp_C]/1 mL; IRIS TENAX WHOLE 12 [hp_C]/1 mL; LILIUM LANCIFOLIUM WHOLE FLOWERING 12 [hp_C]/1 mL; NARCISSUS PSEUDONARCISSUS FLOWER 12 [hp_C]/1 mL; ROSA DAMASCENA FLOWERING TOP 12 [hp_C]/1 mL; SYRINGA VULGARIS FLOWER 12 [hp_C]/1 mL
INACTIVE INGREDIENTS: WATER; ALCOHOL

DRUG FACTS:

ACTIVE INGREDIENTS:

(in each drop): 1.72% of Arsenicum Album 12X, 15X, Lycopodium Clavatum 12X, 15X, Pulsatilla 12X, 15X; Bellis Perennis 12C, 15C, 18C, 30C, Calendula Officinalis 12C, 15C, 18C, 30C, Camellia Japonica 12C, 15C, 18C, 30C, Chrysanthemum Coronarium 12C, 15C, 18C, 30C, Chrysanthemum Leucanthemum 12C, 15C, 18C, 30C, Convallaria Majalis 12C, 15C, 18C, 30C, Gardenia Jasminoides 12C, 15C, 18C, 30C, Impatiens Glandulifera, Flos 12C, 15C, 18C, 30C, Iris Tenax 12C, 15C, 18C, 30C, Lilium Tigrinum 12C, 15C, 18C, 30C, Narcissus Pseudo-Narcissus 12C, 15C, 18C, 30C, Rosa Damascena 12C, 15C, 18C, 30C, Syringa Vulgaris 12C, 15C, 18C, 30C.

INDICATIONS:

May temporarily relieve symptoms associated with reactions to flowers, such as itchy eyes, sneezing, or headache.**

**Claims based on traditional homeopathic practice, not accepted medical evidence. Not FDA evaluated.

WARNINGS:

If pregnant or breastfeeding, ask a health professional before use.

Keep out of reach of children. In case of overdose, get medical help or contact a Poison Control Center right away.

Do not use if tamper evident seal is broken or missing.

Store in a cool, dry place.

KEEP OUT OF REACH OF CHILDREN:

In case of overdose, get medical help or contact a Poison Control Center right away.

DIRECTIONS:

Adults and children 5 to 10 drops orally, 3 times daily or as otherwise directed by a health care professional. If symptoms persist for more than 7 days, consult your health care professional. Consult a physician for use in children under 12 years of age.

INDICATIONS:

May temporarily relieve symptoms associated with reactions to flowers, such as itchy eyes, sneezing, or headache.**

**Claims based on traditional homeopathic practice, not accepted medical evidence. Not FDA evaluated.

INACTIVE INGREDIENTS:

Demineralized water, 20% Ethanol.

QUESTIONS:

Dist. by Energique, Inc.

201 Apple Blvd.

Woodbine, IA 51579 800.869.8078

PACKAGE LABEL DISPLAY:

ENERGIQUE
SINCE 1987
HOMEOPATHIC REMEDY
FLOWER ANTIGENS
1 fl. oz. (30 ml)